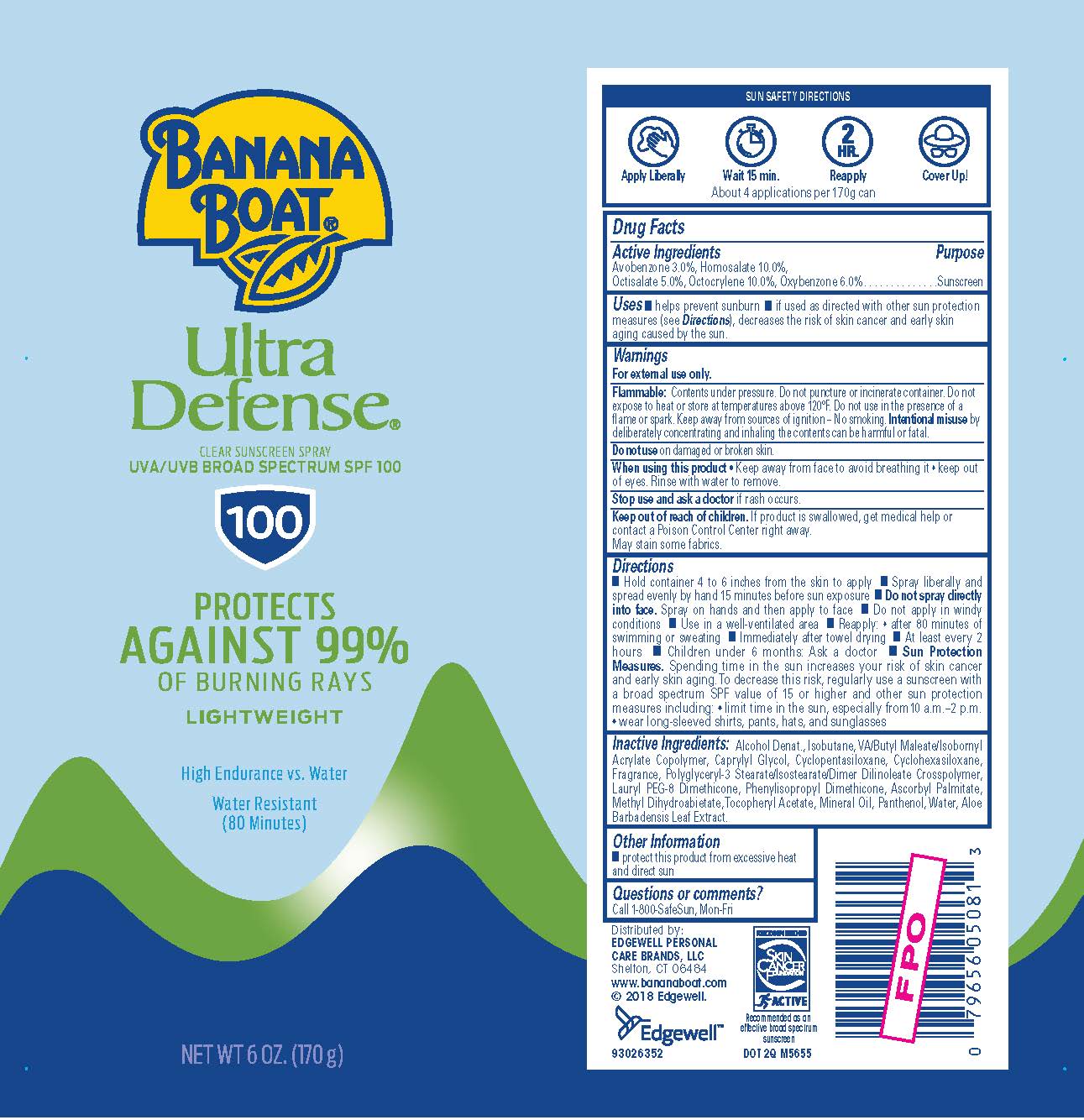 DRUG LABEL: Banana Boat Ultra Defense Clear Sunscreen Broad Spectrum SPF 100
NDC: 63354-751 | Form: SPRAY
Manufacturer: Edgewell Personal Care Brands LLC
Category: otc | Type: HUMAN OTC DRUG LABEL
Date: 20231128

ACTIVE INGREDIENTS: HOMOSALATE 10 g/100 g; OXYBENZONE 6 g/100 g; OCTOCRYLENE 10 g/100 g; AVOBENZONE 3 g/100 g; OCTISALATE 5 g/100 g
INACTIVE INGREDIENTS: WATER; ALCOHOL; ISOBUTANE; ASCORBYL PALMITATE; LAURYL PEG/PPG-18/18 METHICONE; METHYL DIHYDROABIETATE; .ALPHA.-TOCOPHEROL ACETATE; MINERAL OIL; ALOE VERA LEAF; CAPRYLYL GLYCOL; CYCLOMETHICONE 5; PANTHENOL; CYCLOMETHICONE 6

Active ingredients

Avobenzone 3.0%, Homosalate 10.0%, Octisalate 5.0%, Octocrylene 10.0%, Oxybenzone 6.0%

Purpose

Sunscreen

Uses

• helps prevent sunburn • if used as directed with other sun protection measures (see Directions), decreases the risk of skin cancer and early skin aging caused by the sun

Warnings

For external use only

Flammable: Contents under pressure. Do not puncture or incinerate container. Do not expose to heat or store at temperatures above 120°F. Do not use in the presense of a flame or spark. Keep away from sources of ignition - No smoking. Intentional misuse by deliberately concentrating and inhaling the contents can be harmful or fatal

May stain some fabrics

Do not use

on damaged or broken skin

When using this product

• Keep away from face to avoid breathing it • Keep out of eyes. Rinse with water to remove.

Stop use and ask a doctor

if rash occurs

Keep out of reach of children

If product is swallowed, get medical help or contact a Poison Control Center right away.

Directions

• Hold container 4 to 6 inches from the skin to apply • spray liberally and spread evenly by hand 15 minutes before sun exposure • Do not spray directly into face. Spray on hands then apply to face. • Do not apply in windy conditions • Use in well-ventilated area • Reapply: • after 80 minutes of swimming or sweating • immediately after towel drying • at least every 2 hours • Children under 6 months: Ask a doctor

• Sun Protection Measures. Spending time in the sun increases your risk of skin cancer and early skin aging. To decrease this risk, regularly use a sunscreen with a broad spectrum SPF value of 15 or higher and other sun protection measures including: • limit time in the sun, especially from 10 a.m. - 2 p.m. • wear long-sleeved shirts, pants, hats, and sunglasses

Inactive ingredients

Alcohol Denat., Isobutane, VA/Butyl Maleate/Isobornyl Acrylate Copolymer, Caprylyl Glycol, Cyclopentasiloxane, Cyclohexasiloxane, Fragrance, Polyglycerly-3 Stearate/Isostearate/Dimer Dilinoleate Crosspolymer, Lauryl PEG-8 Dimethicone, Phenylisopropyl Dimethicone, Ascorbyl Palmitate, Methyl Dihydroabietate, Tocopheryl Acetate, Mineral Oil, Panthenol, Water, Aloe Barbadensis Leaf Extract

Other information

• protect this product from excessive heat and direct sun

Questions or comments?

Call 1-800-SafeSun, Mon-Fri

Primary Display Panel

BANANA

BOAT (R)

Ultra

Defense (R)

CLEAR SUNSCREEN SPRAY

UVA/UVB BROAD SPECTRUM SPF 100

100

PROTECTS

AGAINST 99%

OF BURNING RAYS

LIGHTWEIGHT

High Endurance vs. Water

Water Resistant

(80 Minutes)

NET WT 6 OZ. (170 g)